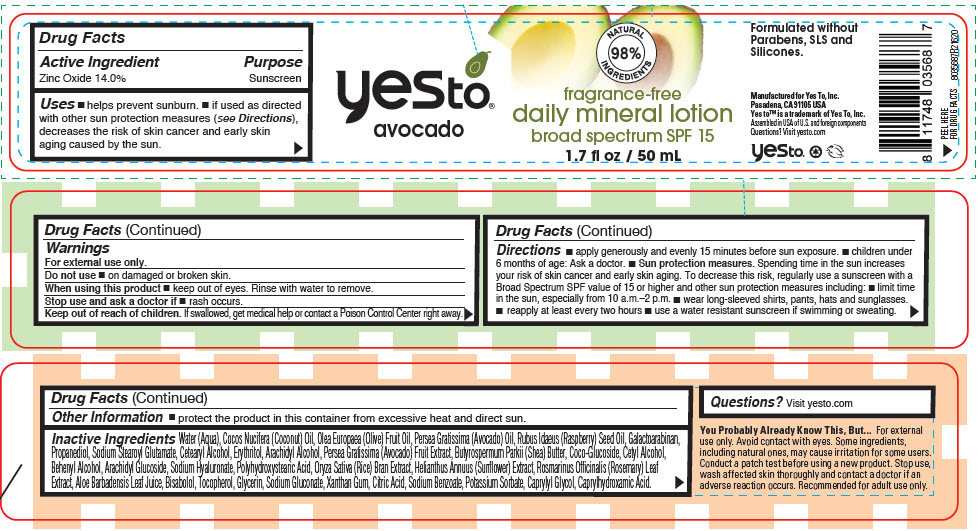 DRUG LABEL: Yes To Avocado Fragrance-Free Daily Mineral Broad Spectrum SPF-15
NDC: 69840-022 | Form: CREAM
Manufacturer: Yes To, Inc.
Category: otc | Type: HUMAN OTC DRUG LABEL
Date: 20201217

ACTIVE INGREDIENTS: Zinc Oxide 140 mg/1 mL
INACTIVE INGREDIENTS: water; ALOE VERA LEAF; Sodium Benzoate; Potassium Sorbate; CITRIC ACID MONOHYDRATE; Propanediol; Xanthan Gum; HYALURONATE SODIUM; Erythritol; Galactoarabinan; Sodium Gluconate; Sodium Stearoyl Glutamate; Caprylhydroxamic Acid; Caprylyl Glycol; Glycerin; COCONUT OIL; OLIVE OIL; AVOCADO OIL; RASPBERRY SEED OIL; SHEA BUTTER; LEVOMENOL; .ALPHA.-BISABOLOL, (+/-)-; RICE BRAN; HELIANTHUS ANNUUS FLOWERING TOP; ROSEMARY; Tocopherol; Cetyl Alcohol; CETOSTEARYL ALCOHOL; COCO GLUCOSIDE; Arachidyl Alcohol; DOCOSANOL; Arachidyl Glucoside; AVOCADO

Yes To® Avocado Fragrance-Free Daily Mineral Lotion Broad Spectrum SPF-15

Drug Facts

Active Ingredient

Zinc Oxide 14.0%

Purpose

Sunscreen

Uses

- helps prevent sunburn.
- if used as directed with other sun protection measures (see Directions), decreases the risk of skin cancer and early skin aging caused by the sun.

Warnings

For external use only.

Do not use

- on damaged or broken skin.

When using this product

- keep out of eyes. Rinse with water to remove.

Stop use and ask a doctor if

- rash occurs.

Keep out of reach of children. If swallowed, get medical help or contact a Poison Control Center right away.

Directions

- apply generously and evenly 15 minutes before sun exposure.
- children under 6 months of age: Ask a doctor.
- Sun protection measures. Spending time in the sun increases your risk of skin cancer and early skin aging. To decrease this risk, regularly use a sunscreen with a Broad Spectrum SPF value of 15 or higher and other sun protection measures including:
  - limit time in the sun, especially from 10 a.m.–2 p.m.
  - wear long-sleeved shirts, pants, hats and sunglasses.
  - reapply at least every two hours
  - use a water resistant sunscreen if swimming or sweating.

Other Information

- protect the product in this container from excessive heat and direct sun.

Inactive Ingredients

Water (Aqua), Cocos Nucifera (Coconut) Oil, Olea Europaea (Olive) Fruit Oil, Persea Gratissima (Avocado) Oil, Rubus Idaeus (Raspberry) Seed Oil, Galactoarabinan, Propanediol, Sodium Stearoyl Glutamate, Cetearyl Alcohol, Erythritol, Arachidyl Alcohol, Persea Gratissima (Avocado) Fruit Extract, Butyrospermum Parkii (Shea) Butter, Coco-Glucoside, Cetyl Alcohol, Behenyl Alcohol, Arachidyl Glucoside, Sodium Hyaluronate, Polyhydroxystearic Acid, Oryza Sativa (Rice) Bran Extract, Helianthus Annuus (Sunflower) Extract, Rosmarinus Officinalis (Rosemary) Leaf Extract, Aloe Barbadensis Leaf Juice, Bisabolol, Tocopherol, Glycerin, Sodium Gluconate, Xanthan Gum, Citric Acid, Sodium Benzoate, Potassium Sorbate, Caprylyl Glycol, Caprylhydroxamic Acid.

Questions?

Visit yesto.com

PRINCIPAL DISPLAY PANEL - 50 mL Jar Label

yes to®
avocado

NATURAL
INGREDIENTS
98%

fragrance-free
daily mineral lotion
broad spectrum SPF 15

1.7 fl oz / 50 mL